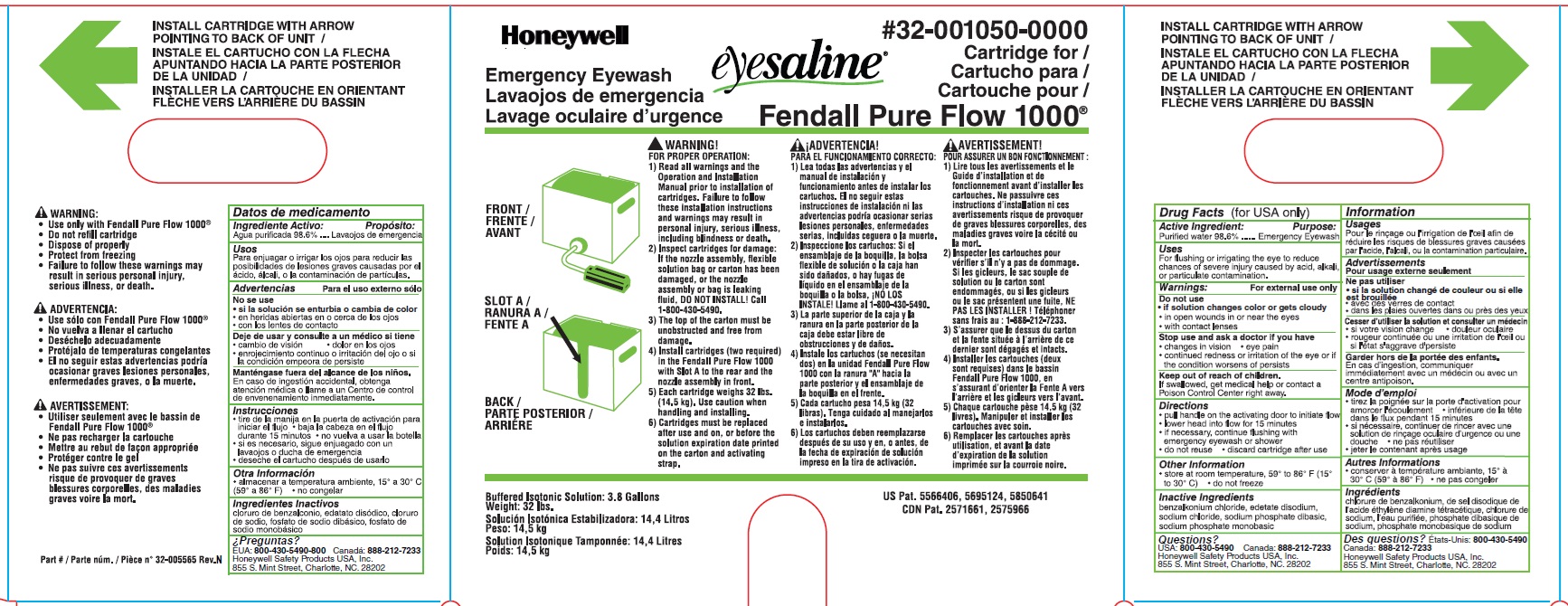 DRUG LABEL: Fendall Pure Flow
NDC: 0498-0630 | Form: LIQUID
Manufacturer: Honeywell Safety Products USA, Inc.
Category: otc | Type: HUMAN OTC DRUG LABEL
Date: 20241210

ACTIVE INGREDIENTS: WATER 98.6 L/100 L
INACTIVE INGREDIENTS: SODIUM CHLORIDE; SODIUM PHOSPHATE, MONOBASIC, MONOHYDRATE; SODIUM PHOSPHATE, DIBASIC; EDETATE DISODIUM; BENZALKONIUM CHLORIDE

PN: 32-001050-0000-H5, NDC: 0498-0630-37: Fendall Pure Flow 1000

Active ingredient

Purified Water 98.6%

Purpose

Emergency Eyewash

Uses

For flushing or irrigating the eye to reduce chances of severe injury caused by acid, alkali, or particulate contamination

Warnings

For external use only

Do not use

- if solution changes color or gets cloud
- in open wounds in or near eyes
- with contact lenses

Stop use and ask a doctor if you have

- changes in vision
- eye pain
- continued redness or irritation of the eyes or if the condition worsens or persists

Keep out of reach of children

If swallowed, get medical help or contact a Poison Control Center right away

Directions

- pull handle on the activation door to initiate flow
- lower head into flow for 15 minutes
- if necessary continue flushing with emergency eyewash or shower
- do not reuse
- discard cartridge after use

Other information

- store at rom temperature, 59o to 86o F (15o to 30o C)
- do not freeze

Inactive ingredients

benzlkonium chloride, edetate disodium, sodium chloride, sodium phosphate dibasic, sodium phosphate monobasic

Questions?

USA: 800-430-5490 Canada: 888-212-7233

Honeywell Safety Products USA, Inc.

855 S. Mint Street, Charlotte, NC, 28202

Changes from previous version

- Indications and Usage
- Warnings and Precautions